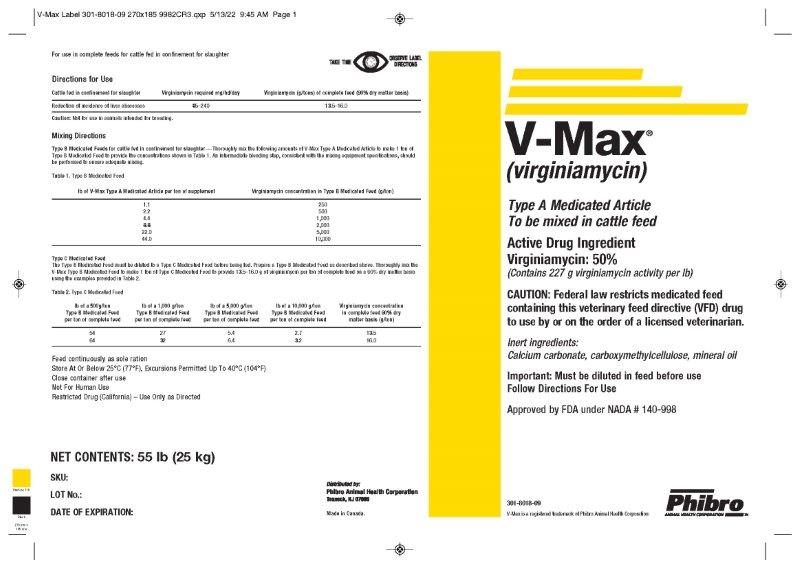 DRUG LABEL: V-Max
NDC: 66104-8902 | Form: POWDER
Manufacturer: Phibro Animal Health
Category: animal | Type: VFD TYPE A MEDICATED ARTICLE ANIMAL DRUG LABEL
Date: 20231108

ACTIVE INGREDIENTS: VIRGINIAMYCIN 227 g/0.45 kg
INACTIVE INGREDIENTS: CALCIUM CARBONATE; MINERAL OIL; CARBOXYMETHYLCELLULOSE SODIUM, UNSPECIFIED FORM; SOYBEAN OIL; RICE BRAN

V-MaxTM
(Virginiamycin)
TYPE A MEDICATED ARTICLE

DESCRIPTION

To be mixed in cattle feed

Active Drug Ingredient

Virginiamycin : 50%

(Contains 227 g virginiamycin activity per lb)

CAUTION

CAUTION: Federal law restricts medicated feed containing this veterinary feed directive (VFD) drug to use by or on the order of a licensed veterinarian.

Inert ingredients:

Calcium carbonate, carboxymethylcellulose, mineral oil

Important: Must be diluted in feed before use

Follow Directions For Use

Approved by FDA under NADA # 140-998

301-8018-09

V-Max is a registered trademark Phibro Animal Health Corporation

NET CONTENTS: 100 lb (45.3 kg)

Distributed by:

PHIBRO ANIMAL HEALTH CORPORATION

Teaneck, NJ 07666, USA

Made in Canada

For use in complete feeds for cattle fed in confinement for slaughter Directions for Use

Cattle fed in confinement for slaughter | Virginiamycin required mg/hd/day | Virginiamycin (g/tons) of complete feed (90% dry matter basis)
Reduction of incidence of liver abscesses | 85–240 | 13.5–16.0
Caution: Not for use in animals intended for breeding.

Mixing Directions

Type B Medicated Feeds for cattle fed in confinement for slaughter—Thoroughly mix the following amounts of V-Max Type A Medicated Article to make 1 ton of Type B Medicated Feed to provide the concentrations shown in Table 1. An intermediate blending step, consistent with the mixing equipment specifications, should be performed to ensure adequate mixing.

Table 1. Type B Medicated Feed

lb of V-Max Type A Medicated Article per ton of supplement | Virginiamycin concentration in Type B Medicated Feed (g/ton)
1.1; 2.2; 4.4; 8.8; 22.0; 44.0 | 250; 500; 1,000; 2,000; 5,000; 10,000

Type C Medicated Feed

The Type B Medicated Feed must be diluted to a Type C Medicated Feed before being fed. Prepare a Type B Medicated Feed as described above. Thoroughly mix the V-Max Type B Medicated Feed to make 1 ton of Type C Medicated Feed to provide 13.5 – 16.0 g of virginiamycin per ton of complete feed on a 90% dry matter basis using the examples provided in Table 2.

Table 2. Type C Medicated Feed

lb of a 500g/ton Type B Medicated Feed per ton of complete feed | lb of a 1,000 g/ton Type B Medicated Feed per ton of complete feed | lb of a 5,000 g/ton Type B Medicated Feed per ton of complete feed | lb of a 10,000 g/ton Type B Medicated Feed per ton of complete feed | Virginiamycin concentration in complete feed 90% dry matter basis (g/ton)
54 | 27 | 5.4 | 2.7 | 13.5
64 | 32 | 6.4 | 3.2 | 16.0

INDICATIONS AND USAGE

NOT FOR HUMAN USE

RESTRICTED DRUG (CALIFORNIA) – USE ONLY AS DIRECTED

VMax Label